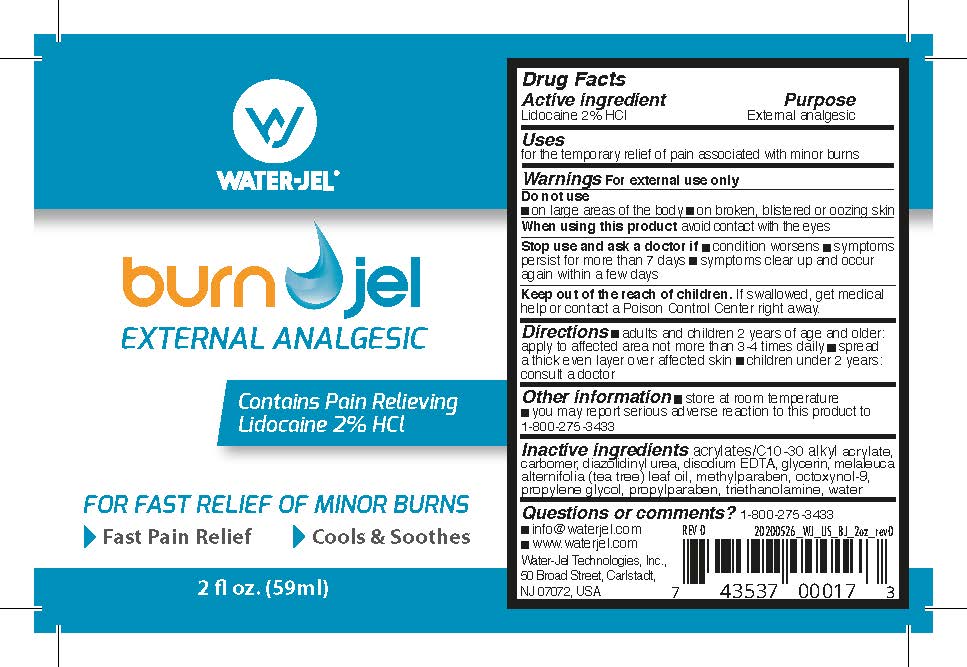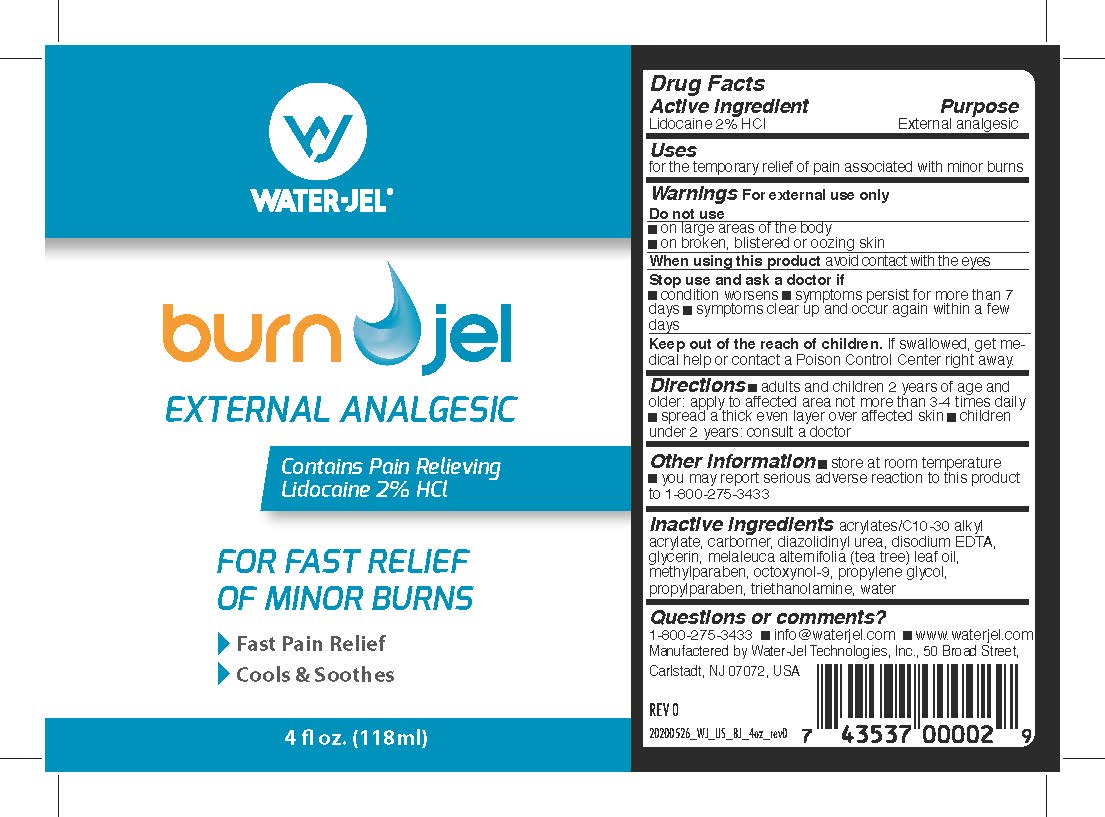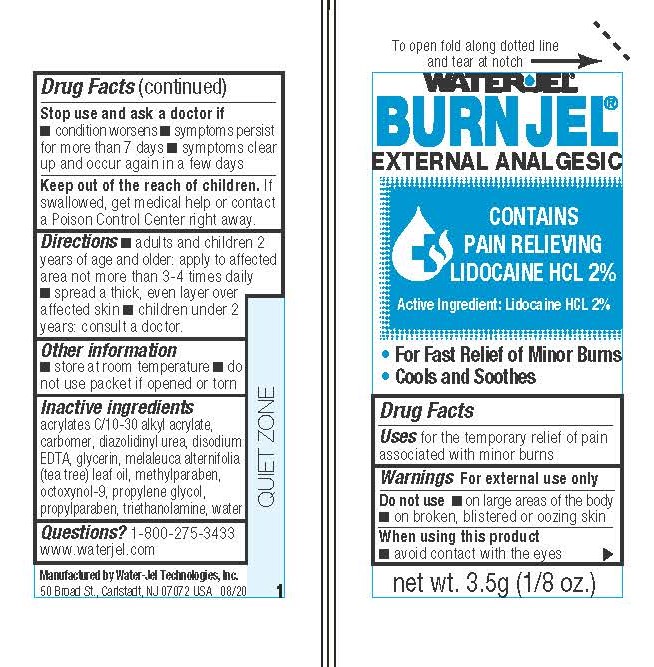 DRUG LABEL: Burn Jel
NDC: 59898-200 | Form: GEL
Manufacturer: Water-Jel Technologies
Category: otc | Type: HUMAN OTC DRUG LABEL
Date: 20250106

ACTIVE INGREDIENTS: LIDOCAINE HYDROCHLORIDE 2 g/100 mL
INACTIVE INGREDIENTS: CARBOMER HOMOPOLYMER TYPE C; GLYCERIN; PROPYLENE GLYCOL; METHYLPARABEN; TEA TREE OIL; DIAZOLIDINYL UREA; TROLAMINE; OCTOXYNOL-9; CARBOMER HOMOPOLYMER TYPE B; PROPYLPARABEN; EDETATE DISODIUM

Burn Jel

Active ingredient

Lidocaine HCl 2.0 %

Purpose

External analgesic

Uses

for the temporary relief of pain associated with minor burns

Warnings

For external use only

Do not use

- on large areas of the body
- on broken, blistered or oozing skin

When using this product

- avoid contact with eyes

Stop use and ask a doctor if

- conditions worsens
- symptoms persist for more than 7 days
- condition clears up and occurs again within a few days

Keep out of the reach of children

If swallowed, get medical help or contact a Poison Control Center right away.

Directions

- adults and children 2 years of age and older; apply to affected area not more than 3 to 4 times daily
- spread a thick even layer over affected skin
- children under 2 years of age: consult a doctor

Other information

- store at room temperature
- you may report a serious adverse reaction to this product to 800-275-3433

Inactive ingredients

acrylates/C10-30 alkyl acrylate, carbomer, diazolidinyl urea, disodium EDTA, glycerin, melaleuca alternifolia (tea tree) leaf oil, methylparaben, octoxynol-9, propylene glycol, propylparaben, triethanolamine, water

Questions or comments?

1-800-275-3433 info@waterjel.com www.waterjel.com
Manufactered by Water-Jel Technologies, Inc., 50 Broad Street,
Carlstadt, NJ 07072, USA